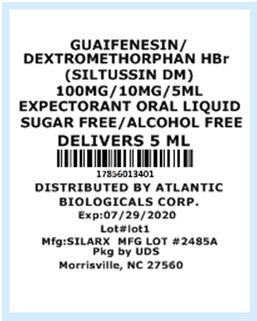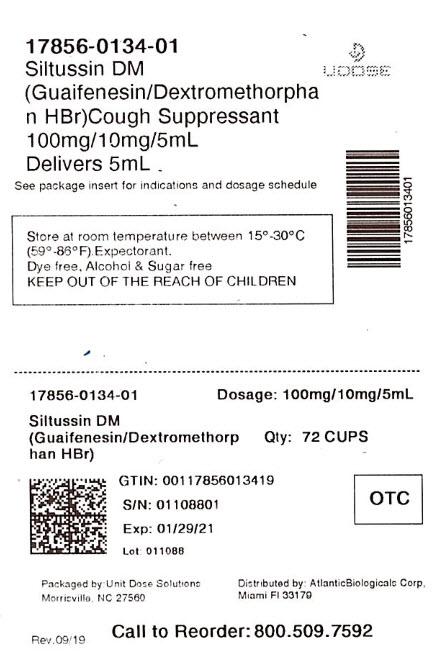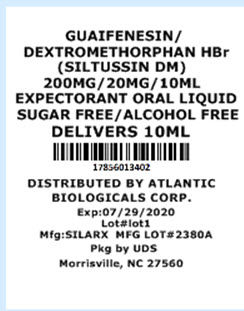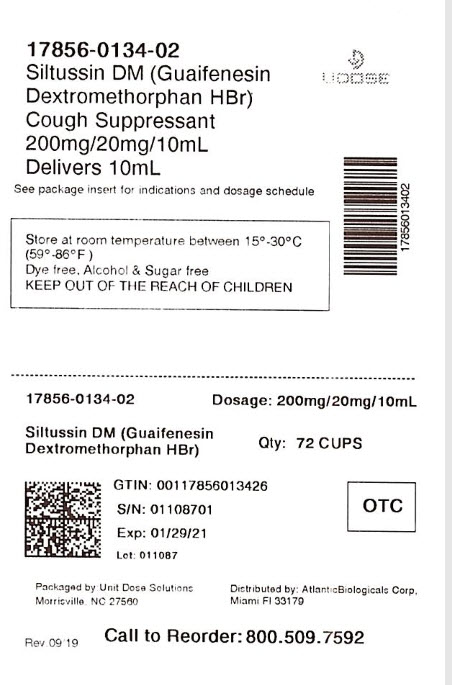 DRUG LABEL: Siltussin DM DAS Cough Formula
NDC: 17856-0134 | Form: LIQUID
Manufacturer: ALTANTIC BIOLOGICALS CORP.
Category: otc | Type: HUMAN OTC DRUG LABEL
Date: 20200729

ACTIVE INGREDIENTS: GUAIFENESIN 100 mg/5 mL; DEXTROMETHORPHAN HYDROBROMIDE 10 mg/5 mL
INACTIVE INGREDIENTS: ANHYDROUS CITRIC ACID; GLYCERIN; MENTHOL; METHYLPARABEN; PROPYLENE GLYCOL; SACCHARIN SODIUM; SODIUM BENZOATE; SORBITOL; WATER

Siltussin DM DAS Cough Formula

Active Ingredient: Guaifenesin 100 mg (in each 5 mL (teaspoonful)(TSP))

Active Ingredient: Dextromethorphan HBr 10 mg (in each 5 mL (teaspoonful)(TSP))

Purpose of Guaifenesin: Expectorant

Purpose of Dextromethorphan HBr: Cough Suppressant

Uses

- temporarily relieves cough due to minor throat and bronchial irritation
- helps loosen phlegm (mucus)
- thin bronchial secretions to make coughs more productive

Warnings

Do not use if you are now taking a prescription monoamine oxidase inhibitor (MAOI) (certain drugs for depression, psychiatric or emotional conditions, or Parkinson’s disease), or for 2 weeks after stopping the MAOI drug. If you do not know if your prescription drug contains an MAOI, ask a doctor or pharmacist before taking this product.

Ask a doctor before use if you have

- persistent cough or chronic cough such as occurs with smoking, asthma, chronic bronchitis, emphysema
- cough accompanied by excessive phlegm (mucus)

Stop use and ask a doctor if

- cough lasts more than 7 days or occurs with fever, rash, or headaches that lasts. This could be signs of a serious condition
- hypersensitive to any ingredients

PREGNANCY OR BREAST FEEDING

If pregnant or breast-feeding, ask a health professional before use.

Keep out of reach of children. In case of overdose, get medical help or contact a Poison Control Center right away.

Directions

- take every 4 hours, or as directed by a doctor
- do not take more than 6 doses in 24 hours

Adults and children 12 years and over | 2 teaspoonfuls (TSP)(10 mL)
Children under 12 years | DO NOT USE

Other information
store at room temperature between 15°-30°C (59°-86°F)

Inactive ingredients

citric acid, strawberry flavor, glycerin, menthol, methylparaben, propylene glycol, saccharin sodium, sodium benzoate, sorbitol, water.

Questions

1-844-834-0530

* This product is not manufactured or distributed by Whitehall Robins, distributor of Robitussin®-DM.

Manufactured by:
Silarx Pharmaceuticals, Inc.
Carmel, NY 10512

10-1042 Rev. 03/18

DISTRIBUTED BY:

ATLANTIC BIOLOGICALS CORP.

20101 N.E 16TH PLACE

MIAMI, FL 33179